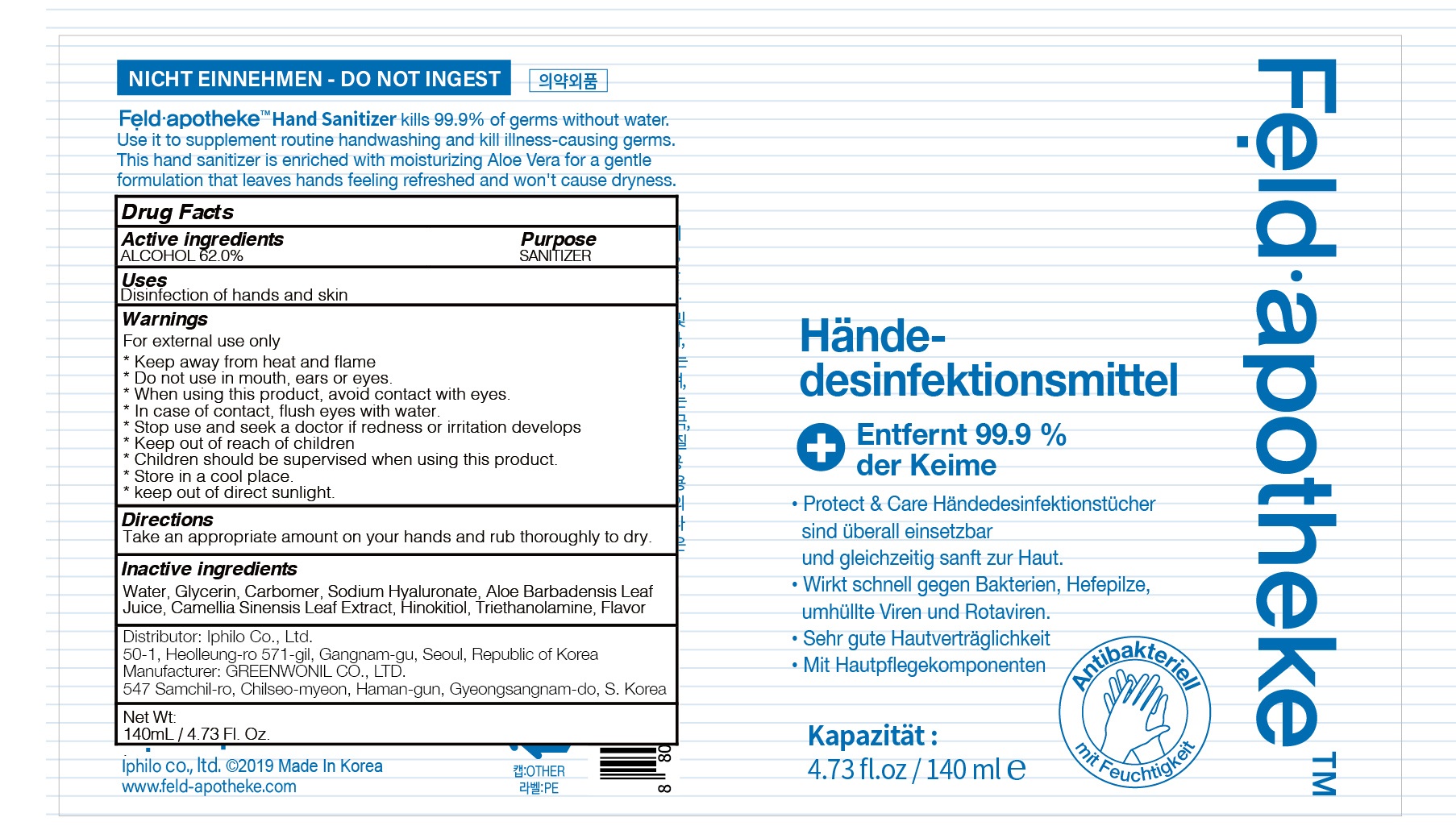 DRUG LABEL: Feld apotheke hand sanitizer
NDC: 74381-010 | Form: GEL
Manufacturer: Iphilo
Category: otc | Type: HUMAN OTC DRUG LABEL
Date: 20200406

ACTIVE INGREDIENTS: ALCOHOL 86.8 g/140 mL
INACTIVE INGREDIENTS: Water; Glycerin; CARBOMER HOMOPOLYMER, UNSPECIFIED TYPE; HYALURONATE SODIUM; ALOE VERA LEAF; TROLAMINE; GREEN TEA LEAF; .BETA.-THUJAPLICIN

ACTIVE INGREDIENT

Active ingredients: ALCOHOL 62%

INACTIVE INGREDIENT

Inactive ingredients:

Water, Glycerin, Carbomer, Sodium Hyaluronate, Aloe Barbadensis Leaf Juice,
Camellia Sinensis Leaf Extract, Hinokitiol, Triethanolamine, Flavor

PURPOSE

Purpose:SANITIZER

WARNINGS

For external use only

* Keep away from heat and flame
* Do not use in mouth, ears or eyes.
* When using this product, avoid contact with eyes.
* In case of contact, flush eyes with water.
* Stop use and seek a doctor if redness or irritation develops
* Keep out of reach of children
* Children should be supervised when using this product.
* Store in a cool place.
* keep out of direct sunlight.

KEEP OUT OF REACH OF CHILDREN

Uses

Disinfection of hands and skin

Directions

Take an appropriate amount on your hands and rub thoroughly to dry.